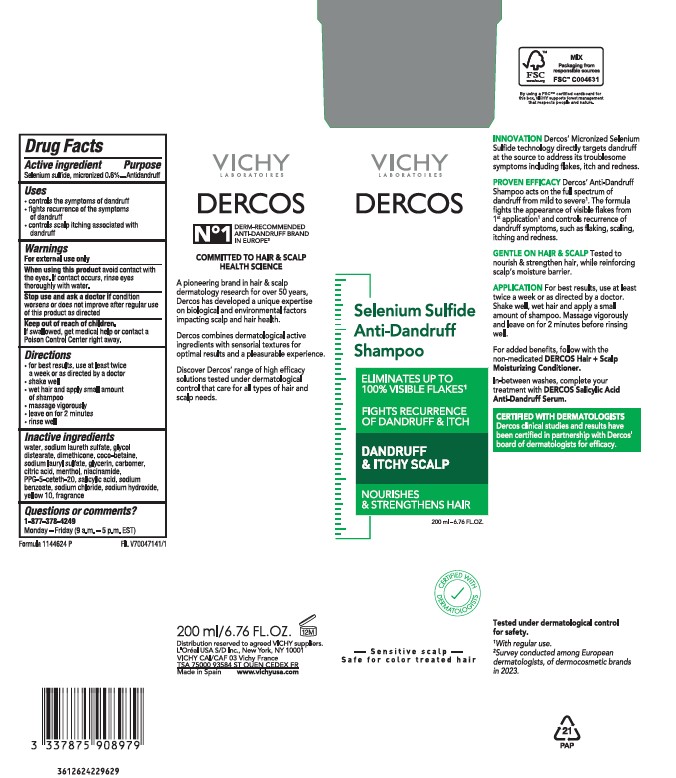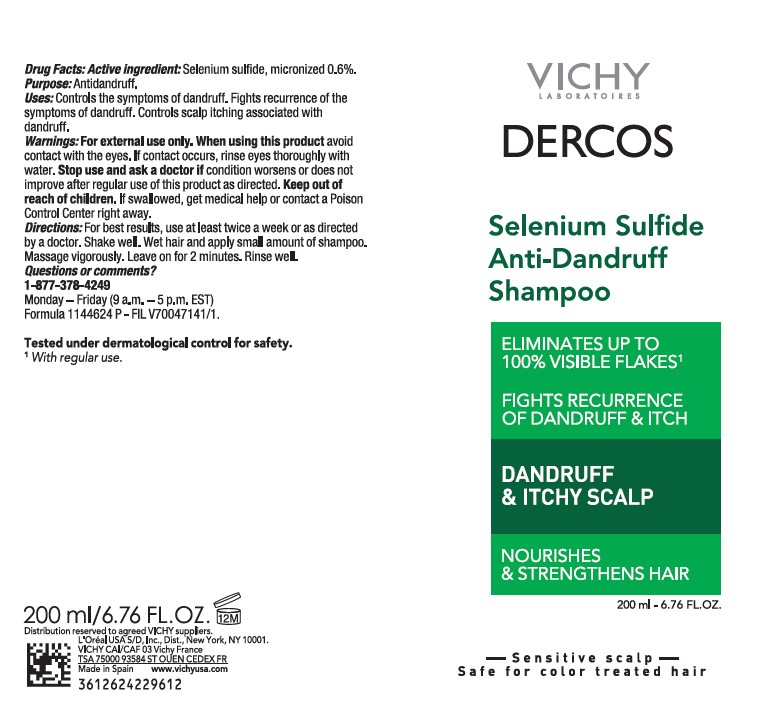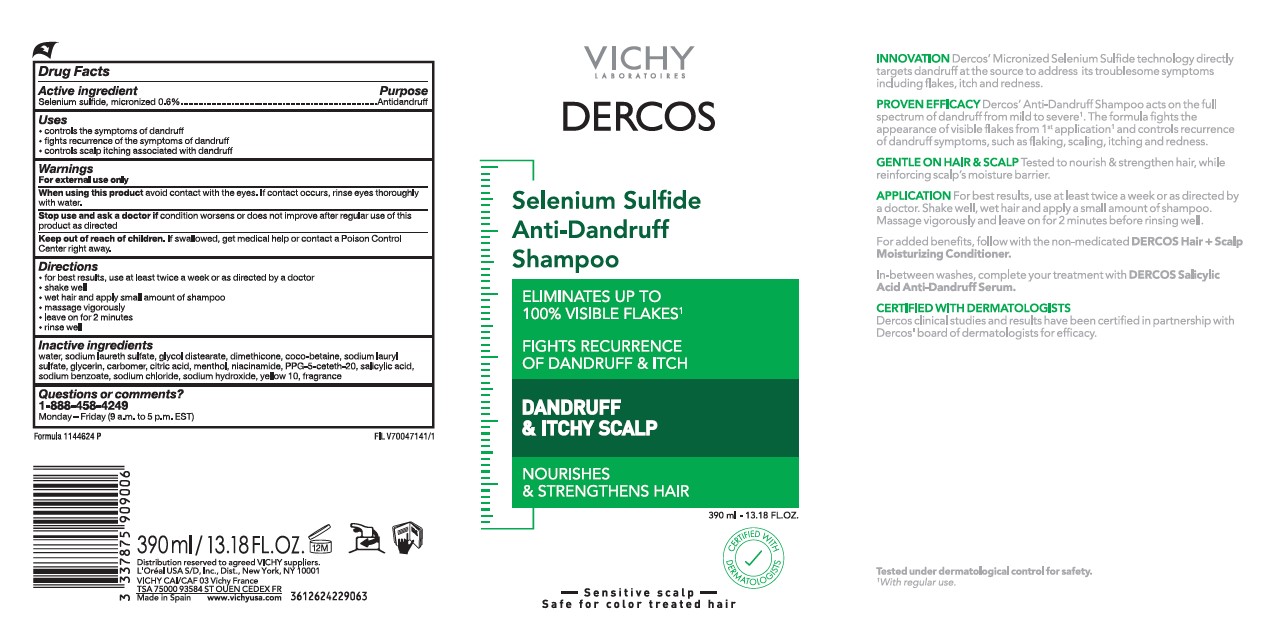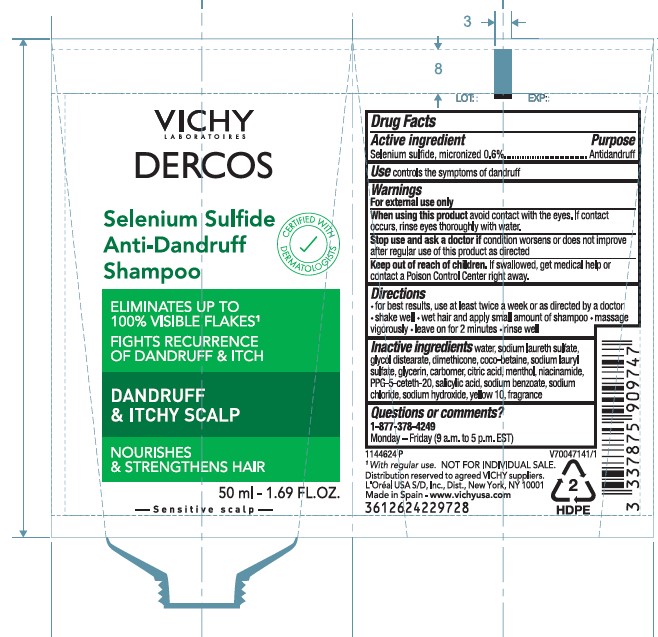 DRUG LABEL: VICHY LABORATOIRES Dercos Selenium Sulfide Anti-dandruff
NDC: 83342-974 | Form: SHAMPOO
Manufacturer: PRODUCTOS CAPILARES L'OREAL SA
Category: otc | Type: HUMAN OTC DRUG LABEL
Date: 20240625

ACTIVE INGREDIENTS: SELENIUM SULFIDE 6 mg/1 mL
INACTIVE INGREDIENTS: Water; SODIUM LAURETH SULFATE; GLYCOL DISTEARATE; DIMETHICONE; COCO-BETAINE; Sodium Lauryl Sulfate; GLYCERIN; CARBOMER HOMOPOLYMER, UNSPECIFIED TYPE; CITRIC ACID MONOHYDRATE; MENTHOL; NIACINAMIDE; PPG-5-CETETH-20; SALICYLIC ACID; SODIUM BENZOATE; SODIUM CHLORIDE; SODIUM HYDROXIDE; D&C YELLOW NO. 10

Drug Facts

Active ingredient

Selenium sulfide, micronized 0.6%

Purpose

Antidandruff

Uses

- controls the symptoms of dandruff
- fights recurrence of the symptoms of dandruff
- controls scalp itching associated with dandruff

Warnings

For external use only

When using this product

avoid contact with the eyes. If contact occurs, rinse eyes thoroughly with water.

Stop use and ask a doctor if

condition worsens or does not improve after regular use of this product as directed

Keep out of reach of children.

If swallowed, get medical help or contact a Poison Control Center right away.

Directions

- for best results, use at least twice a week or as directed by a doctor
- shake well
- wet hair and apply small amount of shampoo
- massage vigorously
- leave on for 2 minutes
- rinse well

Inactive ingredients

water, sodium laureth sulfate, glycol distearate, dimethicone, coco-betaine, sodium lauryl sulfate, glycerin, carbomer, citric acid, menthol, niacinamide, PPG-5-ceteth-20, salicylic acid, sodium benzoate, sodium chloride, sodium hydroxide, yellow 10, fragrance

Question or comments?

1-877-378-4249

Monday - Friday (9 a.m. to 5 p.m. EST)